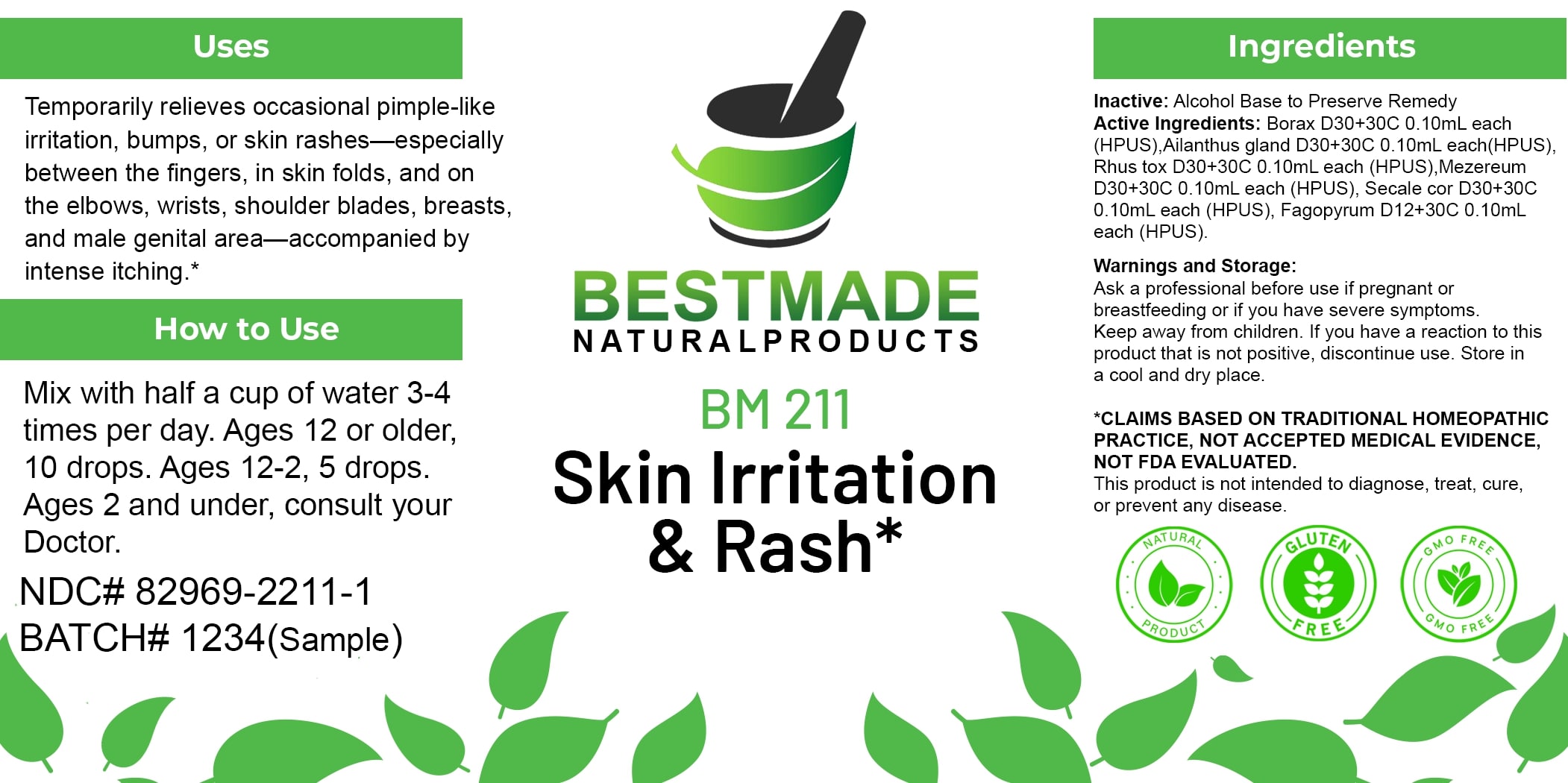 DRUG LABEL: Bestmade Natural Products BM211
NDC: 82969-2211 | Form: LIQUID
Manufacturer: Bestmade Natural Products
Category: homeopathic | Type: HUMAN OTC DRUG LABEL
Date: 20250228

ACTIVE INGREDIENTS: DAPHNE MEZEREUM BARK 30 [hp_C]/30 [hp_C]; AILANTHUS ALTISSIMA FLOWERING TWIG 30 [hp_C]/30 [hp_C]; TOXICODENDRON PUBESCENS LEAF 30 [hp_C]/30 [hp_C]; CLAVICEPS PURPUREA SCLEROTIUM 30 [hp_C]/30 [hp_C]; SODIUM BORATE 30 [hp_C]/30 [hp_C]; FAGOPYRUM ESCULENTUM WHOLE 30 [hp_C]/30 [hp_C]
INACTIVE INGREDIENTS: ALCOHOL 30 [hp_C]/30 [hp_C]

BM211

DOSAGE AND ADMINISTRATION

How to Use

Mix with half a cup of water 3-4 times per day. Ages 12 or older, 10 drops. Ages 12-2, 5 drops. Ages 2 and under, consult your Doctor.

Uses

Temporarily relieves occasional pimple-like irritation, bumps, or skin rashes—especially between the fingers, in skin folds, and on the elbows, wrists, shoulder blades, breasts, and male genital area—accompanied by intense itching.*

*CLAIMS BASED ON TRADITIONAL HOMEOPATHIC PRACTICE, NOT ACCEPTED MEDICAL EVIDENCE, NOT FDA EVALUATED.

This product is not intended to diagnose, treat, cure, or prevent any disease.

Inactive:

Alcohol Base to Preserve Product

ACTIVE INGREDIENT

Active Ingredients: Borax D30+30C 0.10mL each (HPUS), Ailanthus gland D30+30C 0.10mL each (HPUS), Rhus tox D30+30C 0.10mL each (HPUS), Mezereum D30+30C 0.10mL each (HPUS), Secale cor D30+30C 0.10mL each (HPUS), Fagopyrum D12+30C 0.10mL each (HPUS).

KEEP OUT OF REACH OF CHILDREN

Warnings and Storage:

Ask a professional before use if pregnant or breastfeeding or if you have severe symptoms. Keep away from children. If you have a reaction to this product that is not positive, discontinue use. Store in a cool and dry place.

Warnings and Storage:

Ask a professional before use if pregnant or breastfeeding or if you have severe symptoms. Keep away from children. If you have a reaction to this product that is not positive, discontinue use. Store in a cool and dry place.

*CLAIMS BASED ON TRADITIONAL HOMEOPATHIC PRACTICE, NOT ACCEPTED MEDICAL EVIDENCE, NOT FDA EVALUATED. This product is not intended to diagnose, treat, cure, or prevent any disease.

Uses

Temporarily relieves occasional pimple-like irritation, bumps, or skin rashes—especially between the fingers, in skin folds, and on the elbows, wrists, shoulder blades, breasts, and male genital area—accompanied by intense itching.*

*CLAIMS BASED ON TRADITIONAL HOMEOPATHIC PRACTICE, NOT ACCEPTED MEDICAL EVIDENCE, NOT FDA EVALUATED.

This product is not intended to diagnose, treat, cure, or prevent any disease.

Entire package label